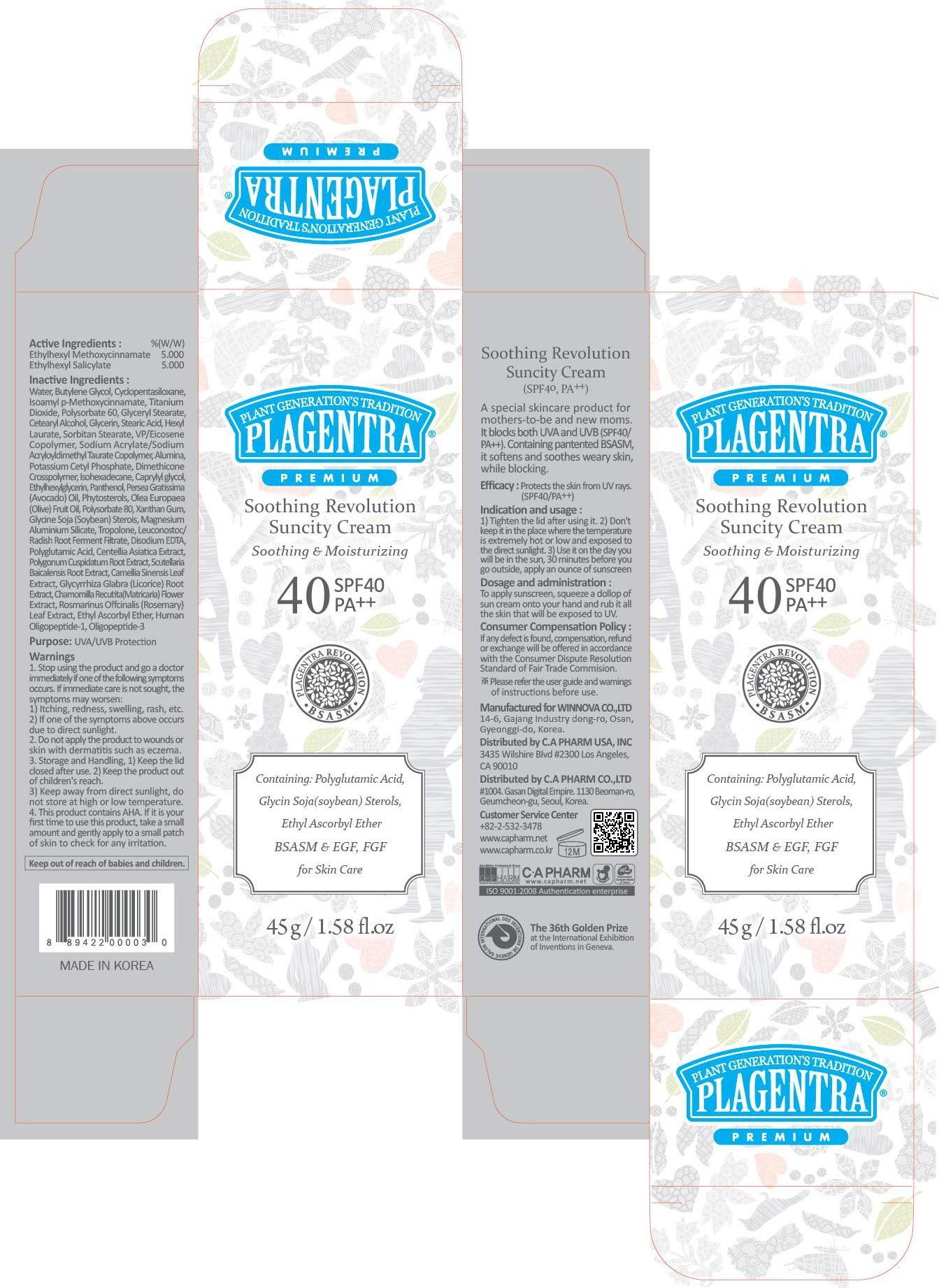 DRUG LABEL: PLAGENTRA SOOTHING REVOLUTION SUNCITY
NDC: 68988-120 | Form: CREAM
Manufacturer: C.A Pharm Co., Ltd.
Category: otc | Type: HUMAN OTC DRUG LABEL
Date: 20141205

ACTIVE INGREDIENTS: OCTINOXATE 2.25 g/45 g; OCTISALATE 2.25 g/45 g
INACTIVE INGREDIENTS: Water; Butylene Glycol

ACTIVE INGREDIENT

Active Ingredients: ETHYLHEXYL METHOXYCINNAMATE 5.0%, ETHYLHEXYL SALICYLATE 5.0%

INACTIVE INGREDIENT

Inactive Ingredients:
Water, Butylene Glycol, Cyclopentasiloxane, Isoamyl p-Methoxycinnamate, Titanium Dioxide, Polysorbate 60, Glyceryl Stearate, Cetearyl Alcohol, Glycerin, Stearic Acid, Hexyl Laurate, Sorbitan Stearate, VP/Eicosene Copolymer, Sodium Acrylate/Sodium Acryloyldimethyl Taurate Copolymer, Alumina, Potassium Cetyl Phosphate, Dimethicone Crosspolymer, Isohexadecane, Caprylyl glycol, Ethylhexylglycerin, Panthenol, Persea Gratissima (Avocado) Oil, Phytosterols, Olea Europaea (Olive) Fruit Oil, Polysorbate 80, Xanthan Gum, Glycine Soja (Soybean) Sterois, Magnesium Aluminium Silicate, Tropolone, Leuconostoc/Radish Root Ferment Filtrate, Disodium EDTA, Polyglutamic Acid, Centellia Asiatica Extract, Polygonum Cuspidatum Root Extract, Scutellaria Baicalensis Root Extract, Camellia Sinensis Leaf Extract, Glycyrrhiza Glabra (Licorice) Root Extract, Chamomilla Recutita(Matricaria) Flower Extract, Rosmarinus Offcinalis (Rosemary) Leaf Extract, Ethyl Ascorbyl Ether, Human Oligopeptide-1, Oligopeptide-3

PURPOSE

Purpose: UVA/UVB Protection

WARNINGS

1. Stop using the product and go to a doctor immediately if one of the following symptoms occurs. If immediate care is not sought, the symptoms may worsen :
1) Itching, redness, swelling, rash, etc. 2) If one of the symptoms above occurs due to direct sunlight.
2. Do not apply the product to wounds or skin with dermatitis such as eczema.
3. Storage and Handling, 1) Keep the lid closed after use. 2) Keep the product out of children's reach. 3) Keep away from direct sunlight, do not store at high or low temperature.
4. It contains AHA. If it is your first time to use this product, take a small amount and gently apply to the skin to check if it cause andy trouble to your skin.

KEEP OUT OF REACH OF CHILDREN

Keep out of reach of babies and children.

INDICATIONS & USAGE

Indication and usage:
1) Tighten the lid after using it.
2) Don't keep it in the place where the temperature is extremely hot or low and exposed to the direct sunlight.
3) Use it on the day you will be in the sun, 30 minutes before you go outside, apply on ounce of sunscreen.

DOSAGE & ADMINISTRATION

Dosage and administration:
To apply sunscreen, squeeze a dollop of sun cream onto your hand and rub it all the skin that will be exposed to UV.